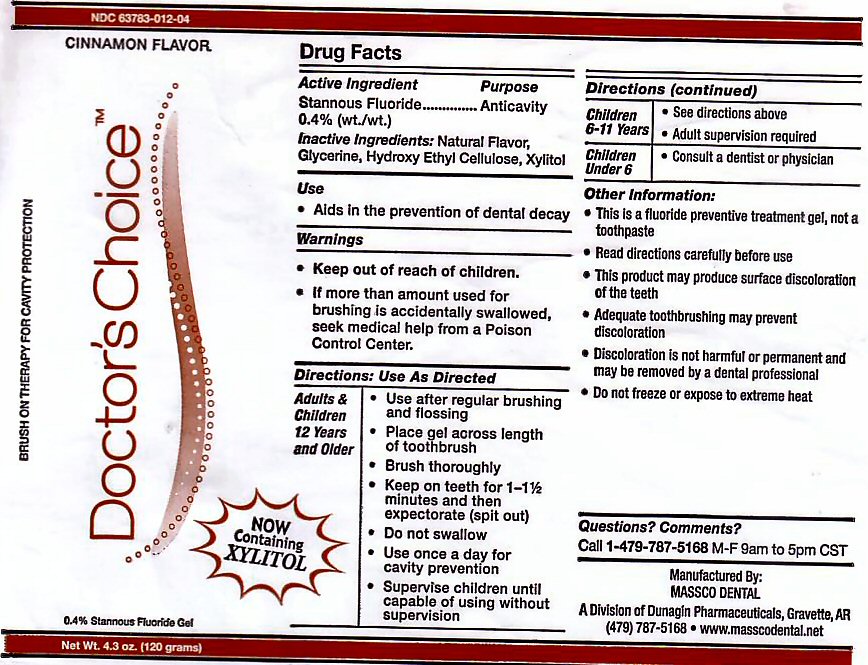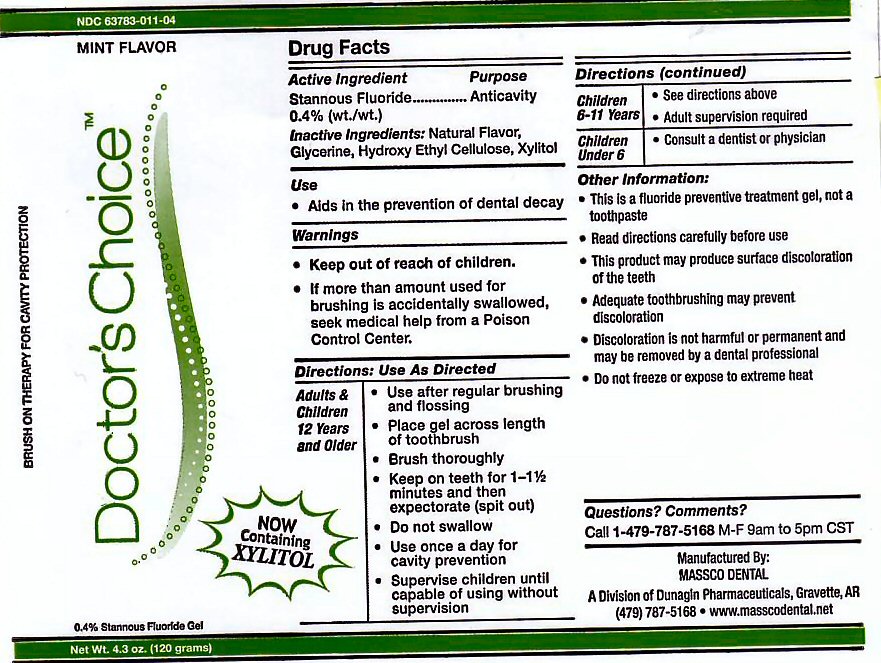 DRUG LABEL: DOCTORS CHOICE
NDC: 63783-011 | Form: GEL, DENTIFRICE
Manufacturer: Massco Dental A Division of Dunagin Pharmaceuticals
Category: prescription | Type: HUMAN PRESCRIPTION DRUG LABEL
Date: 20251211

ACTIVE INGREDIENTS: STANNOUS FLUORIDE 0.12 g/120 g
INACTIVE INGREDIENTS: GLYCERIN; HYDROXYETHYL CELLULOSE (2000 CPS AT 1%); XYLITOL

ACTIVE INGREDIENT

Active Ingredient: Stannous Fluoride

INACTIVE INGREDIENTS

Glycerine, Hydroxy Ethyl Celluulose, Natural Flavor, Xylitol

USE

Aids in the prevention of dental decay.

KEEP OUT OF REACH OF CHILDREN

DIRECTIONS FOR USE

Adults and Children 12 years and Older: Use after regular brushing and flossing. Place gel across length of toothbrush. Brush Thoroughly. Keep on teeth for 1 - 1 1/2 minutes and then expectorate (spit out). Do not swallow. Use once a day for cavity prevention. Supervise children until capable of using without supervision.

Children 6-11 Years: See directions above. Adult supervision required.

Children Under 6: Consult a Dentist or Physician.

OTHER INFORMATION

This is a fluoride prevention treatment gel, not a toothpaste. Read directions carefully before use. This product may produce surface discoloration of the teeth. Adequate toothbrushing may prevent discoloration. Discoloration is not harmful or permanent and may be removed by a dental professional. Do not freeze or expose to extreme heat.

QUESTIONS ? COMMENTS ?

Call 1-479-787-5168 M-F 9am to 5pm CST

WARNINGS

If more than amount used for brushing is accidentally swallowed, seek medical help from a poison control center.

PACKAGE LABEL

Brush on Therapy for Cavity Prevention - Doctor's Choice 0.4% Stannous Fluoride Gel

Manufactured by Massco Dental

res